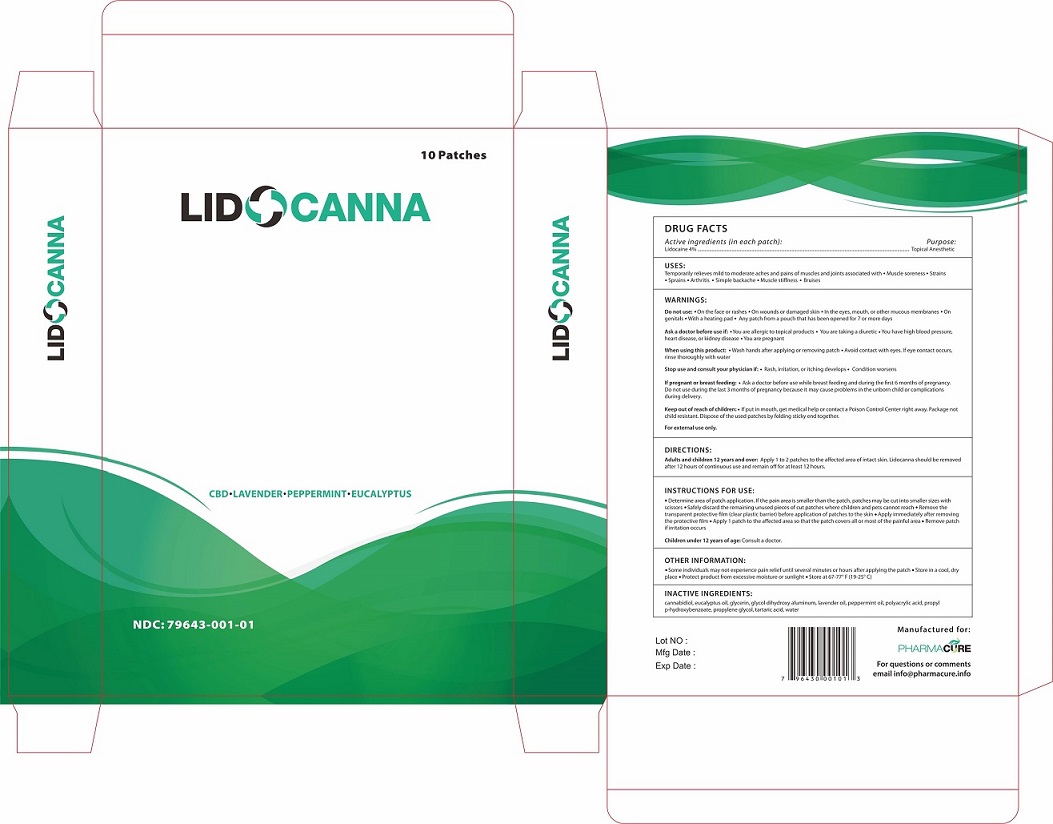 DRUG LABEL: Lidocanna
NDC: 79643-001 | Form: PATCH
Manufacturer: PHARMACURE LLC
Category: otc | Type: HUMAN OTC DRUG LABEL
Date: 20251006

ACTIVE INGREDIENTS: LIDOCAINE 4 g/100 g
INACTIVE INGREDIENTS: WATER; CANNABIDIOL; EUCALYPTUS OIL; GLYCERIN; LAVENDER OIL; PEPPERMINT OIL; POLYACRYLIC ACID (250000 MW); PROPYLPARABEN; PROPYLENE GLYCOL; TARTARIC ACID

Active Ingredient

Lidocaine 4%

Purpose

Topical Anesthetic

Uses

Temporarily relieves mild to moderate aches and pains of muscles and joints associated with muscle soreness, strains, sprains, arthritis, simple backache, muscle stiffness, bruises.

Warnings

Do not useon the face or rashes, on wounds or damaged skin, in the eyes, mouth, or other mucous membranes, on genitals, with a heating pad, any patch from a pouch that has been opened for 7 or more days.

Ask a doctorbefore use if you are allergic to topical products, you are taking a diuretic, you have high blood pressure, heart disease, kidney disease, or you are pregnant.

When using this productwash hands after applying or removing patch. Avoid contact with eyes. If eye contact occurs, rinse thoroughly with water.

Stop use and consult your physician ifrash, irritation, or itching develops, or condition worsens.

If pregnant or breastfeeding, ask a doctor before use while breastfeeding and during the first 6 months of pregnancy. Do not use during the last 3 months of pregnancy because it may cause problems in the unborn child or complications during delivery.

For external use only

Keep out of reach of children.If product is put in mouth, get medical help of contact a Poison Control Center right away. Package is not child resistant. Dispose of the used patches by folding sticky ends together.

Directions

Adults and children 12 years and over: apply 1 to 2 patches to the affected area of intact skin. Lidocanna should be removed after 12 hours of continuous use and remain off for at least 12 hours.

Inactive ingredients

Cannabidiol, eucalyptus oil, glycerin, glycol dihydroxy aluminum, lavender oil, peppermint oil, polyacrylic acid, propyl p-hydroxybenzoate, propylene glycol, tartaric acid, water

Other information

Some individuals may not experience pain relief until several minutes or hours after applying the patch. Store in a cool, dry place. Protect the product from excessive moisture or sunlight. Store at 67-77°F (19-25°C).